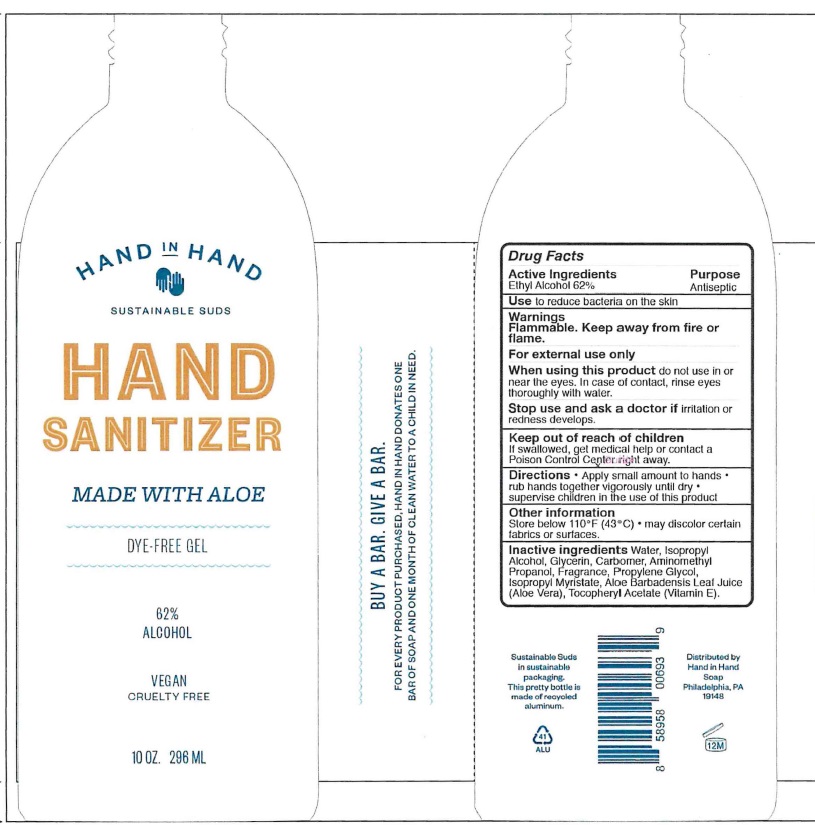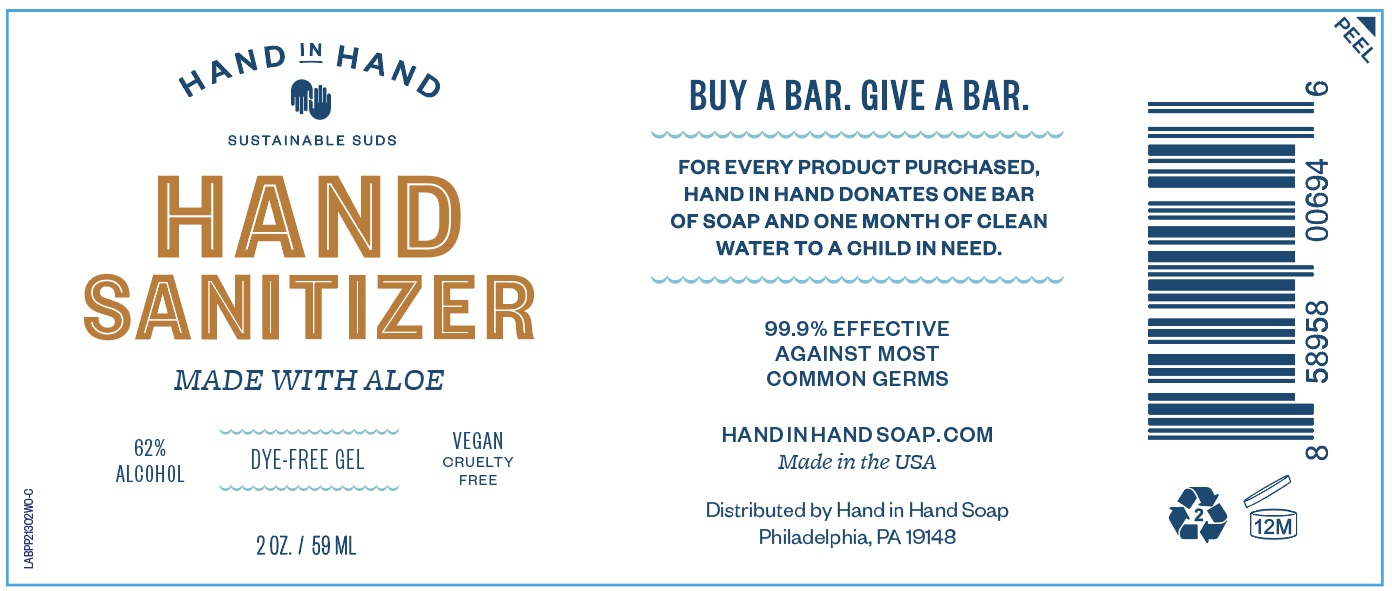 DRUG LABEL: Hand In Hand
NDC: 74687-062 | Form: LIQUID
Manufacturer: HAND IN HAND SOAP LLC
Category: otc | Type: HUMAN OTC DRUG LABEL
Date: 20220128

ACTIVE INGREDIENTS: ALCOHOL 62 mL/100 mL
INACTIVE INGREDIENTS: WATER; ISOPROPYL ALCOHOL; GLYCERIN; CARBOMER HOMOPOLYMER, UNSPECIFIED TYPE; AMINOMETHYLPROPANOL; PROPYLENE GLYCOL; ISOPROPYL MYRISTATE; ALOE VERA LEAF; .ALPHA.-TOCOPHEROL ACETATE

Hand Sanitizer

Active Ingredient

Ethyl Alcohol 62%

Purpose

Antiseptic

Use

To reduce bacteria on the skin

Warnings

Flammable, Keep away from fire or flame.

For external use only.

When using this product

do not use in or near the eyes. In case of contact, rinse eye thoroughly with water

Stop use and ask a doctor if

irritation or redness develops

Keep out of reach of children

If swallowed, get medical help or contact or contact a Poison Control Center right away

Directions

- Apply small amounts to hands rub hands vigorously until dry
- supervise children in the use of this product

Other information

Store below 110°F (43° C)

may discolor certain fabrics or surfaces

Inactive Ingredients

Water, Isopropyl Alcohol, Glycerin, Carbomer, Aminomethyl Propano, Fragrance, Propylene Glycol, Isopropyl Myristate, Aloe Barbadensis Leaf Juice (Aloe Vera), Tocopheryl Acetate (Vitamin E).

Principal Display Panel

NDC 74687-062-02

HAND IN HAND

SUSTAINABLE SUDS

HAND SANITIZER

MADE WITH ALOE

62% ALCOHOL

DYE-FREE GEL

VEGAN CRUELTY FREE

BUY A BAR. GIVE A BAR.

FOR EVERY PRODUCT PURCHASED, HAND IN HAND DONATES ONE BAR OF SOAP AND ONE MONTH OF CLEAN WATER TO A CHILD IN NEED.

99.9% EFFECTIVE AGAINST MOST COMMON GERMS

HANDINHANDSOAP.COM

Made in the USA

Distributed by Hand in Hand Soap, Philadelphia, PA 19148

2 oz / 59 mL

NDC 74687-062-10

HAND IN HAND

SUSTAINABLE SUDS

HAND SANITIZER

MADE WITH ALOE

62% ALCOHOL

DYE-FREE GEL

VEGAN CRUELTY FREE

BUY A BAR. GIVE A BAR.

FOR EVERY PRODUCT PURCHASED, HAND IN HAND DONATES ONE BAR OF SOAP AND ONE MONTH OF CLEAN WATER TO A CHILD IN NEED.

99.9% EFFECTIVE AGAINST MOST COMMON GERMS

HANDINHANDSOAP.COM

Made in the USA

Distributed by Hand in Hand Soap, Philadelphia, PA 19148

10 oz / 296 mL